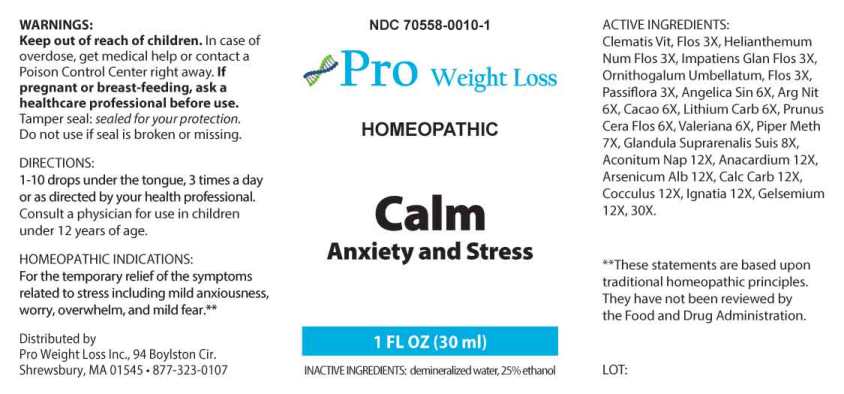 DRUG LABEL: Calm Anxiety and Stress
NDC: 70558-0010 | Form: LIQUID
Manufacturer: Pro Weight Loss Inc.
Category: homeopathic | Type: HUMAN OTC DRUG LABEL
Date: 20230110

ACTIVE INGREDIENTS: CLEMATIS VITALBA FLOWER 3 [hp_X]/1 mL; HELIANTHEMUM NUMMULARIUM FLOWER 3 [hp_X]/1 mL; IMPATIENS GLANDULIFERA FLOWER 3 [hp_X]/1 mL; ORNITHOGALUM UMBELLATUM FLOWERING TOP 3 [hp_X]/1 mL; PASSIFLORA INCARNATA FLOWERING TOP 3 [hp_X]/1 mL; ANGELICA SINENSIS ROOT 6 [hp_X]/1 mL; SILVER NITRATE 6 [hp_X]/1 mL; COCOA 6 [hp_X]/1 mL; LITHIUM CARBONATE 6 [hp_X]/1 mL; PRUNUS CERASIFERA FLOWER 6 [hp_X]/1 mL; VALERIAN 6 [hp_X]/1 mL; MACROPIPER METHYSTICUM ROOT 7 [hp_X]/1 mL; SUS SCROFA ADRENAL GLAND 8 [hp_X]/1 mL; ACONITUM NAPELLUS WHOLE 12 [hp_X]/1 mL; SEMECARPUS ANACARDIUM JUICE 12 [hp_X]/1 mL; ARSENIC TRIOXIDE 12 [hp_X]/1 mL; OYSTER SHELL CALCIUM CARBONATE, CRUDE 12 [hp_X]/1 mL; ANAMIRTA COCCULUS SEED 12 [hp_X]/1 mL; STRYCHNOS IGNATII SEED 12 [hp_X]/1 mL; GELSEMIUM SEMPERVIRENS ROOT 12 [hp_X]/1 mL
INACTIVE INGREDIENTS: WATER; ALCOHOL

DRUG FACTS:

ACTIVE INGREDIENTS:

Clematis Vitalba, Flos 3X, Helianthemum Nummularium, Flos 3X, Impatiens Glandulifera, Flos 3X, Ornithogalum Umbellatum, Flos 3X, Passiflora Incarnata 3X, Angelica Sinensis 6X, Argentum Nitricum 6X, Cacao 6X, Lithium Carbonicum 6X, Prunus Cerasifera, Flos 6X, Valeriana Officinalis 6X, Piper Methysticum 7X, Glandula Suprarenalis Suis 8X, Aconitum Napellus 12X, Anacardium Orientale 12X, Arsenicum Album 12X, Calcarea Carbonica 12X, Cocculus Indicus 12X, Ignatia Amara 12X, Gelsemium Sempervirens 12X, 30X.

HOMEOPATHIC INDICATIONS:

For temporary relief of symptoms related to stress including mild anxiousness, worry, overwhelm, and mild fear.**

**These statements are based upon traditional homeopathic principles. They have not been reviewed by the Food and Drug Administration.

WARNINGS:

Keep out of reach of children. In case of overdose, get medical help or contact a Poison Control Center right away.

If pregnant or breast-feeding, ask a healthcare professional before use.

Tamper seal: sealed for your protection.

Do not use if seal is broken or missing.

Keep out of reach of children. In case of overdose, get medical help or contact a Poison Control Center right away.

DIRECTIONS:

1-10 drops under the tongue, 3 times a day or as directed by your health professional. Consult a physician for use in children under 12 years of age.

HOMEOPATHIC INDICATIONS:

For temporary relief of symptoms related to stress including mild anxiousness, worry, overwhelm, and mild fear.**

**These statements are based upon traditional homeopathic principles. They have not been reviewed by the Food and Drug Administration.

INACTIVE INGREDIENTS:

demineralized water, 25% ethanol

QUESTIONS:

Distributed by

Pro Weight Loss Inc., 94 Boylston Cir.

Shrewsbury, MA 01545 • 877-323-0107

PACKAGE LABEL DISPLAY:

NDC 70558-0010-1
Pro Weight Loss
HOMEOPATHIC
Calm

Anxiety and Stress

1 FL OZ (30 ml)